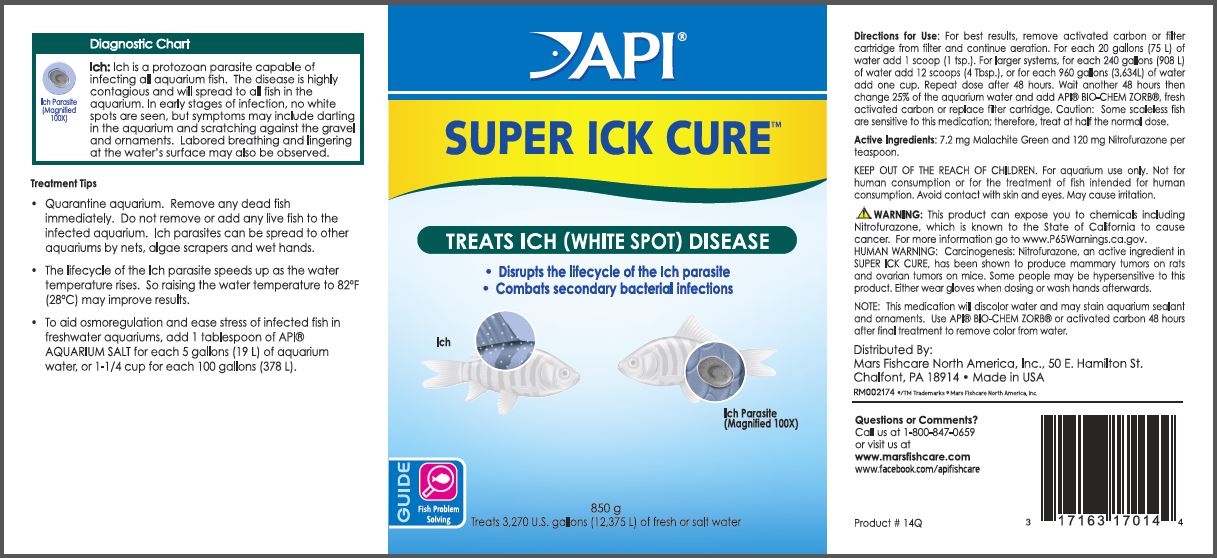 DRUG LABEL: API Super Ick Cure
NDC: 17163-513 | Form: POWDER
Manufacturer: MARS FISHCARE NORTH AMERICA, INC.
Category: animal | Type: OTC ANIMAL DRUG LABEL
Date: 20211229

ACTIVE INGREDIENTS: NITROFURAZONE 120 mg/5.2 g; MALACHITE GREEN 120 mg/5.2 g

Drug Label

ACTIVE INGREDIENT

Active Ingredients: 7.2 mg Malachite Green and 120 mg Nitrofurazone per teaspoon.

DOSAGE AND ADMINISTRATION

Directions for Use:

For best results, remove activated carbon or filter cartridge from filter and continue aeration.

For each 20 gallons (75 L) of water add 1 scoop (1 tsp.). For larger systems, for each 240 gallons (908 L) of water add 12 scoops (4 Tbsp.), or for each 960 gallons (3,634L) of water add one cup. Repeat dose after 48 hours. Wait another 48 hours then change 25% of the aquarium water and add API BIO-CHEM ZORB, fresh activated carbon or replace filter cartridge. Caution: Some scaleless fish are sensitive to this medication; therefore, treat at half the normal dose.

INDICATIONS AND USAGE

Diagnostic Chart

Ich: Ich is a protozoan parasite capable of infecting all aquarium fish. The disease is highly contagious and will spread to all fish in the aquarium. In early stages of infection, no white spots are seen, but symptoms may include darting in the aquarium and scratching against the gravel and ornaments. Labored breathing and lingering at the water's surface may also be observed.

Treatment Tips

Quarantine aquarium. Remove any dead fish immediately. Do not remove or add any live fish to the infected aquarium. Ich parasites can be spread to other aquariums by nets, algae scrapers and wet hands.

The lifecycle of the Ich parasite speeds up as the water temperature rises. So raising the water temperature to 82 F (28 C) may improve results.

To aid osmoregulation and ease stress of infected fish in freshwater aquariums, add 1 tablespoon of API AQUARIUM SALT for each 5 gallons (19 L) of aquarium water, or 1-1/4 cup for each 100 gallons (378 L).

WARNINGS AND PRECAUTIONS

KEEP OUT OF THE REACH OF CHILDREN.

For aquarium use only.

Not for human consumption or for the treatment of fish intended for human consumption.

Avoid contact with skin and eyes.

May cause irritation.

! WARNING:

This product can expose you to chemicals including Nitrofurazone, which is known to the State of California to cause cancer.

For more information go to www.P65Warnings.ca.gov.

HUMAN WARNING:

Carcinogenesis:

Nitrofurazone, an active ingredient in Super Ick Cure, has been shown to produce mammary tumors on rats and ovarian tumors on mice.

Some people may be hypersensitive to this product.

Either wear gloves when dosing or wash hands afterwards.

NOTE: This medication will discolor water and may stain aquarium sealant and ornaments. Use API BIO-CHEM ZORB or activated carbon 48 hours after final treatment to remove color from water.

PACKAGE LABEL

API

SUPER ICK CURE

TREATS ICH (WHITE SPOT) DISEASE

Disrupts the lifecycle of the Ich parasite

Combats secondary bacterial infections

Ich

Ich Parasite (Magnified 100X)

GUIDE

Fish Problem

Solving

850 g

Treats 3,270 U.S. gallons (12,375 L) of fresh or salt water